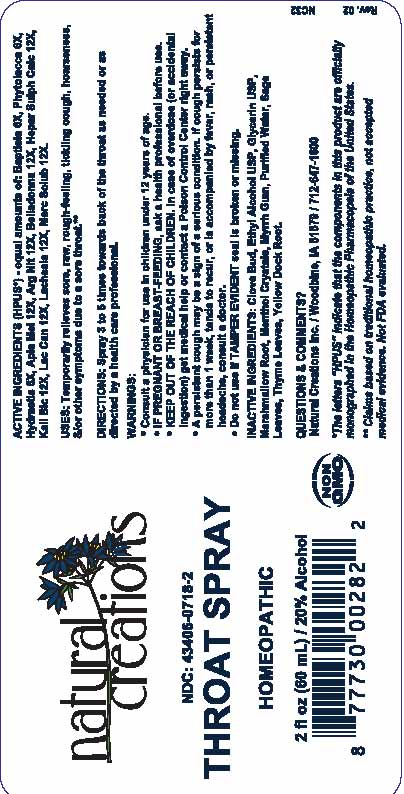 DRUG LABEL: Throat
NDC: 43406-0718 | Form: SPRAY
Manufacturer: Natural Creations, Inc
Category: homeopathic | Type: HUMAN OTC DRUG LABEL
Date: 20251218

ACTIVE INGREDIENTS: BAPTISIA TINCTORIA WHOLE 6 [hp_X]/1 mL; PHYTOLACCA AMERICANA ROOT 6 [hp_X]/1 mL; GOLDENSEAL 6 [hp_X]/1 mL; APIS MELLIFERA 12 [hp_X]/1 mL; SILVER NITRATE 12 [hp_X]/1 mL; ATROPA BELLADONNA 12 [hp_X]/1 mL; CALCIUM SULFIDE 12 [hp_X]/1 mL; POTASSIUM DICHROMATE 12 [hp_X]/1 mL; CANIS LUPUS FAMILIARIS MILK 12 [hp_X]/1 mL; LACHESIS MUTA VENOM 12 [hp_X]/1 mL; MERCURIUS SOLUBILIS 12 [hp_X]/1 mL
INACTIVE INGREDIENTS: clove; GLYCERIN; ALTHAEA OFFICINALIS ROOT; MENTHOL; MYRRH; sage; THYME; RUMEX CRISPUS ROOT; ALCOHOL; WATER

Throat Spray

ACTIVE INGREDIENT

ACTIVE INGREDIENTS (HPUS*) - equal amounts of: Baptisia 6X, Phytolacca 6X, Hydrastis 6X, Apis mel 12X, Arg Nit 12X, Belladonna 12X, Hepar Sulph Calc 12X, Kali Bic 12X, Lac Can 12X, Lachesis 12X, Merc Solub 12X

INDICATIONS AND USAGE

USES: Temporarily relieves sore, raw, rough-feeling, tickling cough, hoarseness, &/or other symptoms due to a sore throat.**

PURPOSE

USES: Temporarily relieves sore, raw, rough-feeling, tickling cough, hoarseness, &/or other symptoms due to a sore throat.**

DOSAGE AND ADMINISTRATION

DIRECTIONS: Spray 3 to 5 times towards back of the throat as needed or as directed by a health care professional.

KEEP OUT OF REACH OF CHILDREN

KEEP OUT OF THE REACH OF CHILDREN. In case of overdose (or accidental ingestion) get medical help or contact a Poison Control Center right away.

WARNINGS:

- Consult a physician for use in children under 12 years of age.
- IF PREGNANT OR BREAST-FEEDING, ask a health care professional before use.
- KEEP OUT OF THE REACH OF CHILDREN. In case of overdose (or accidental ingestion) get medical help or contact a Poison Control Center right away.
- A persistent cough may be a sign of a serious condition. If cough persists for more than 1 week, tends to recur, or is accompanied by fever, rash, or persistent headache, consult a doctor.
- Do not use if TAMPER EVIDENT seal is broken or missing.

INACTIVE INGREDIENT

INACTIVE INGREDIENTS: Clove Bud, Ethyl Alcohol USP, Glycerin USP, Marshmallow Root, Menthol Crystals, Myrrh Gum, Purified Water, Sage leaves, Thyme Leaves, Yellow Dock Root

QUESTIONS & COMMENTS?

Natural Creations, Inc. / Woodbine, IA 51579 / 712-647-1600

REFERENCES

*The letters "HPUS" indicate the components in the product are officially monographed in the Homeopathic Pharmacopeia of the United States.

**Claims based on traditional homeopathic practice, not accepted medical evidence. Not FDA evaluated.

PACKAGE LABEL

NDC:43406-0718-2

Throat Spray

HOMEOPATHIC

2 fl oz (60mL) / 20% Alcohol